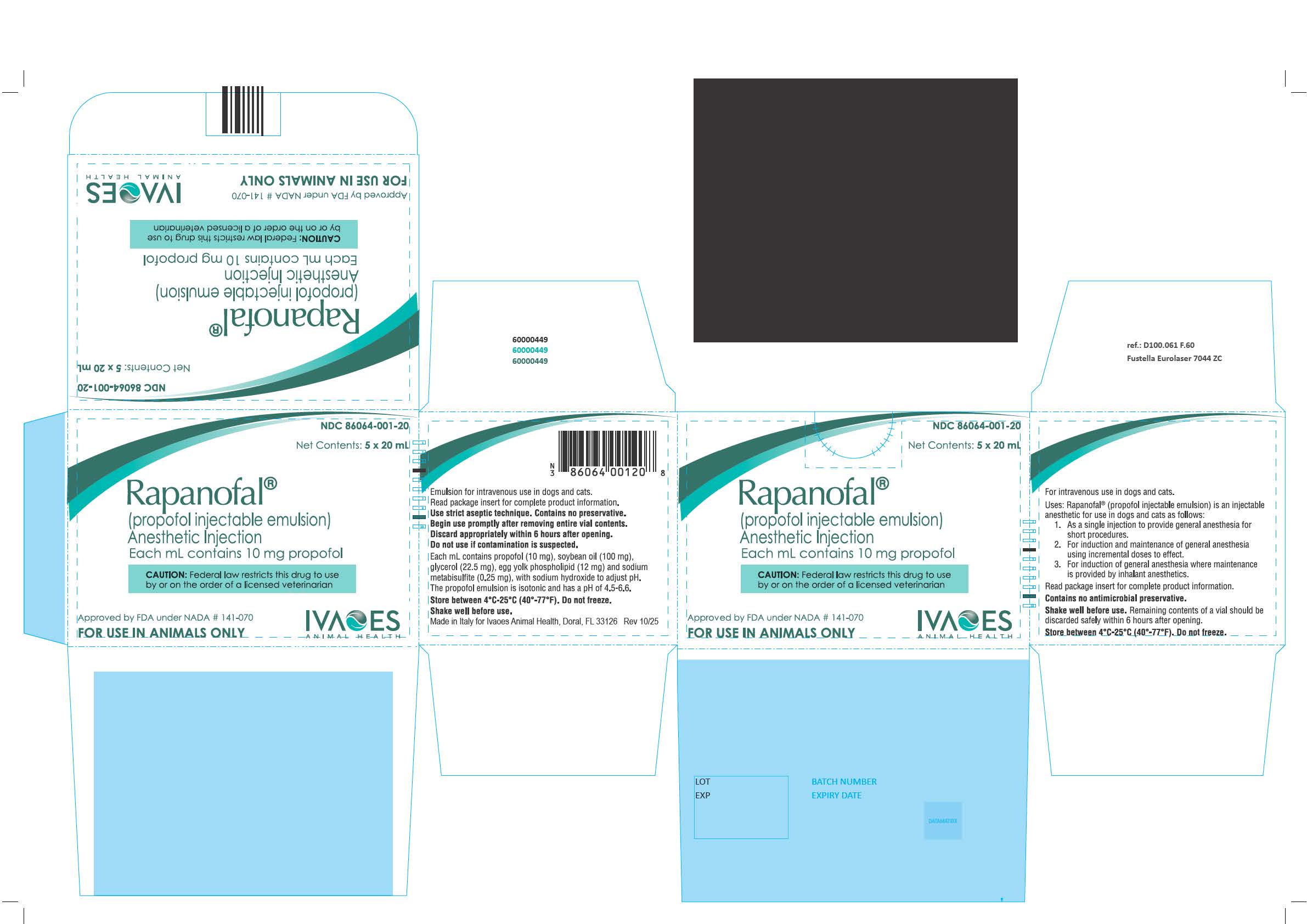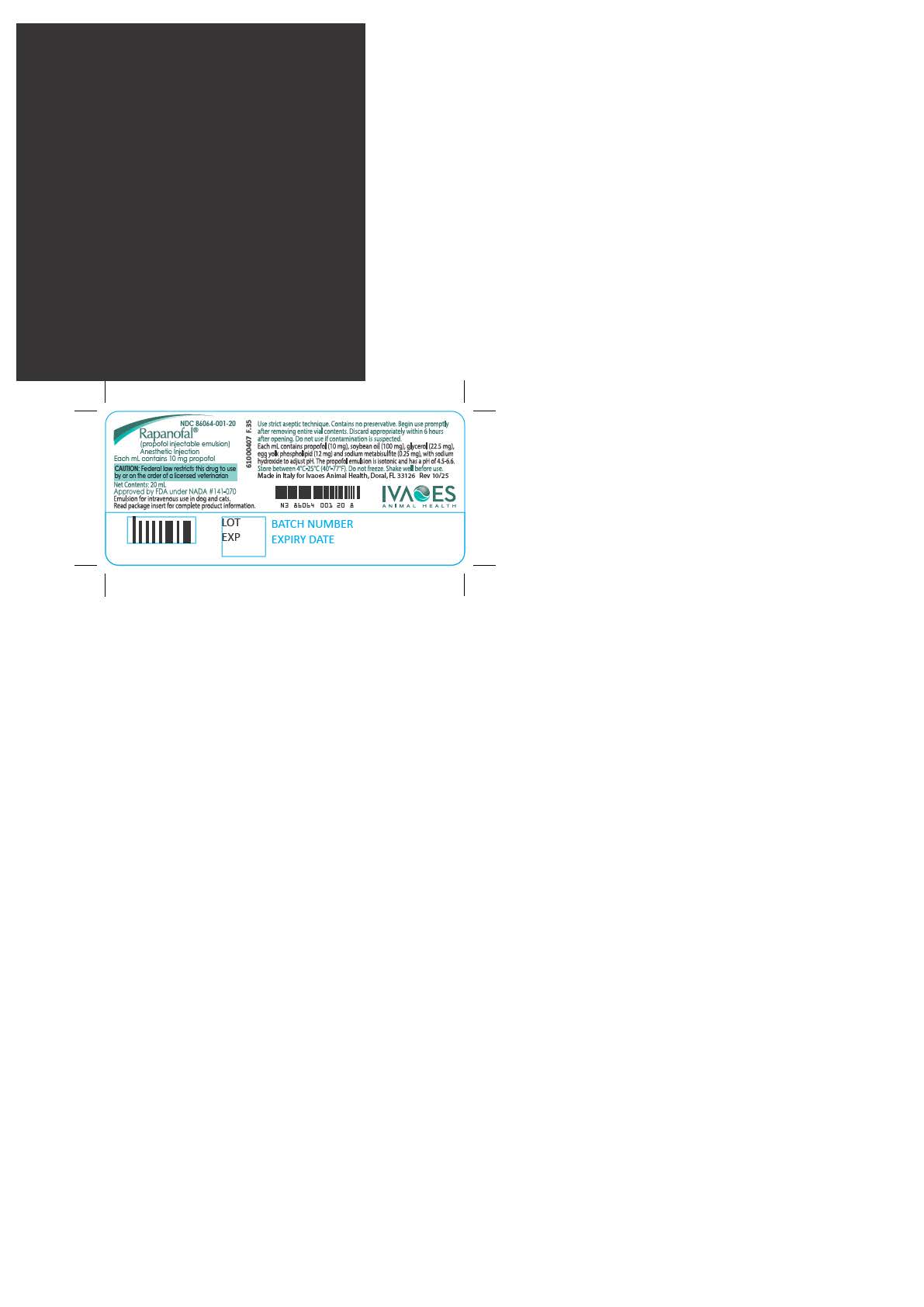 DRUG LABEL: Rapanofal
NDC: 86064-001 | Form: INJECTION, EMULSION
Manufacturer: Ivaoes, LLC
Category: animal | Type: PRESCRIPTION ANIMAL DRUG LABEL
Date: 20251111

ACTIVE INGREDIENTS: PROPOFOL 10 mg/1 mL
INACTIVE INGREDIENTS: SOYBEAN OIL; GLYCERIN; EGG PHOSPHOLIPIDS; SODIUM METABISULFITE; SODIUM HYDROXIDE

Rapanofal®

For Animals Only

Rapanofal®

(propofol injectable emulsion)

Anesthetic Injection

Each mL contains 10 mg propofol.

Approved by FDA under NADA #141-070

Emulsion for intravenous use in dogs and cats.

CAUTION: Federal law restricts this drug to use by or on the order of a licensed veterinarian.

DESCRIPTION

Rapanofal® (propofol) injection is a sterile, nonpyrogenic emulsion containing 10 mg/mL of propofol suitable for intravenous administration. Propofol is chemically described as 2,6- diisopropylphenol and has a molecular weight of 178.28. Propofol is very slightly soluble in water and is therefore formulated as a white, oil-in-water emulsion. Each mL contains propofol (10 mg), soybean oil (100 mg), glycerol (22.5 mg), egg yolk phospholipid (12 mg) and sodium metabisulfite (0.25 mg), with sodium hydroxide to adjust the pH. The propofol emulsion is isotonic and has a pH of 4.5-6.6.

INDICATIONS

Rapanofal® (propofol) is an anesthetic injection for use in dogs and cats as follows:

1. As a single injection to provide general anesthesia for short procedures.

2. For induction and maintenance of general anesthesia using incremental doses to effect.

3. For induction of general anesthesia where maintenance is provided by inhalant anesthetics.

Induction of general anesthesia will usually be observed within 30 to 60 seconds after the end of administration (administration should take 60 to 90 seconds). The doses for induction and maintenance vary depending upon species and preanesthetics. The duration of anesthesia varies depending upon species, dose, and preanesthetics.

In dogs, the duration of anesthesia following the recommended induction dose (5.5 to 7.0 mg/kg without premedication) is generally 5 to 7 minutes. The duration of anesthesia after maintenance doses varies from 2 to 6 minutes following 1.1 mg/kg to 6 to 10 minutes following 3.3 mg/kg. Full standing recovery is generally observed within 10 to 20 minutes after the end of anesthesia, regardless of the duration of anesthesia. Recovery may be delayed in sighthounds or if preanesthetics are administered.

In cats, the duration of anesthesia following the recommended induction dose (8.0 to 13.2 mg/kg without premedication) is generally 5 to 12 minutes. The duration of anesthesia after maintenance doses varies from 5 to 7 minutes following 1.1 mg/kg to 12 to 18 minutes following 4.4 mg/kg. Full standing recovery is generally observed within 30 to 45 minutes after the end of anesthesia, regardless of the duration of anesthesia. Recovery may be delayed if preanesthetics are administered.

DOSAGE AND ADMINISTRATION

Shake the vial thoroughly before opening.

Rapanofal® injection contains no antimicrobial preservatives. Strict aseptic techniques must always be maintained during handling since the vehicle is capable of supporting rapid growth of microorganisms. Failure to follow aseptic handling procedures may result in microbial contamination causing fever, infection/sepsis, and/or other life-threatening illness. Do not use if contamination is suspected.

Rapanofal® injection should be prepared for use just prior to initiation of each individual anesthetic procedure. The vial rubber stopper should be disinfected using 70% isopropyl alcohol. The entire contents of the vial should be drawn into sterile syringes immediately after vials are opened.

Administration should commence promptly and be completed within 6 hours after the vials are opened.

Any unused product should be discarded within 6 hours.

Administer by intravenous injection only.

The emulsion should not be mixed with other therapeutic agents or injected into containers of infusion fluids prior to administration.

INDUCTION OF GENERAL ANESTHESIA

For induction, Rapanofal® injection should be titrated against the response of the patient over approximately 60 to 90 seconds or until clinical signs show the onset of anesthesia.

If Rapanofal® injection is injected too slowly (greater than 90 seconds), an inadequate plane of anesthesia can occur. If this occurs, an additional low dose (1.1 mg/kg) of propofol may be administered to facilitate intubation or the transition to inhalant maintenance anesthesia.

The average induction dose ranges and dosage rates for healthy dogs given propofol alone, or when propofol is preceded by a premedicant, are indicated in the following table (the Table is for guidance only; in practice, the dose should be based upon patient response):

Induction Dosage Guidelines for Dogs
Preanesthetic | Propofol Induction Dose |  | Propofol Rate of Administration
 | mg/kg | mg/lb | Seconds | mg/kg/min | mL/kg/min
None | 5.5-7.0 | 2.5-3.2 | 60-90 | 3.7-7.0 | 0.37-0.70
Acepromazine | 4.0-4.4 | 1.8-2.0 | 60-90 | 2.7-4.4 | 0.27-0.44
Xylazine | 2.2-3.3 | 1.0-1.5 | 60-90 | 1.5-3.3 | 0.15-0.33
Oxymorphone | 2.2-3.3 | 1.0-1.5 | 60-90 | 1.5-3.3 | 0.15-0.33
Medetomidine | 2.2-2.8 | 1.0-1.3 | 60-90 | 1.5-2.8 | 0.15-0.28

The required dose of tranquilizers, sedatives, or analgesics administered as preanesthetic medications (listed below) may be lower than the label directions for their use as a single medication^1.

Acepromazine | 0.03-0.1 | mg/kg | IM, SC, IV
Xylazine | 0.25-0.5 | mg/kg | IV
Xylazine | 0.5-1.0 | mg/kg | IM, SC
Oxymorphone | 0.1-0.2 | mg/kg | IM, SC, IV
Medetomidine | 5.0-10.0 | µg/kg | IM

The use of the drugs listed above as preanesthetics for dogs markedly reduces propofol requirements.

As with other sedative hypnotic agents, the amount of phenothiazine, opioid, and/or alpha-agonist premedication will influence the response of the patient to an induction dose of Rapanofal® injection. The induction dose will also be influenced by the interval between the administration of premedication and induction, and by the rate of administration of propofol.

The average induction dose ranges and dosage rates for healthy cats given propofol alone, or when propofol is preceded by a premedicant, are indicated in the following table (the Table is for guidance only; in practice, the dose should be based upon patient response):

Induction Dosage Guidelines for Cats
Preanesthetic | Propofol Induction Dose |  | Propofol Rate of Administration
 | mg/kg | mg/lb | Seconds | mg/kg/min | mL/kg/min
None | 8.0-13.2 | 3.6-6.0 | 60-90 | 5.3-13.2 | 0.53-1.32
Acepromazine | 8.0-13.2 | 3.6-6.0 | 60-90 | 5.3-13.2 | 0.53-1.32
Butorphanol | 8.0-13.2 | 3.6-6.0 | 60-90 | 5.3-13.2 | 0.53-1.32
Oxymorphone | 8.0-13.2 | 3.6-6.0 | 60-90 | 5.3-13.2 | 0.53-1.32
Xylazine | 7.0-12.0 | 3.2-5.5 | 60-90 | 4.7-12.0 | 0.47-1.20

The required dosage of tranquilizers, sedatives, or analgesics administered as preanesthetic medications (listed below) may be lower than the label directions for their use as a single medication^1,8,9.

Acepromazine | 0.03-0.1 | mg/kg | IM, SC, IV
Butorphanol | 0.1-0.4 | mg/kg | IM, SC
Oxymorphone | 0.1-0.4 | mg/kg | IM, SC, IV
Xylazine | 0.25-0.5 | mg/kg | IV
Xylazine | 0.5-1.0 | mg/kg | IM, SC

The use of the drugs listed above as preanesthetics for cats may reduce propofol requirements. As with other sedative hypnotic agents, the amount of phenothiazine, opioid and/or alpha2-agonist premedication will influence the response of the patient to an induction dose of Rapanofal® injection. The induction dose will also be influenced by the interval between the administration of premedication and induction, and by the rate of administration of propofol.

MAINTENANCE OF GENERAL ANESTHESIA

A.Intermittent Propofol Injections: Anesthesia can be maintained by administering propofol in intermittent IV injections. Clinical response will be determined by the amount, the rate of administration, and the frequency of maintenance injections. The following Tables are provided for guidance:

Maintenance Dosage Guidelines for Dogs
Preanesthetic | Propofol Maintenance Dose |  | Propofol Rate of Administration
 | mg/kg | mg/lb | Seconds | mg/kg/min | mL/kg/min
None | 1.1-3.3 | 0.5-1.5 | 30-60 | 1.1-3.3 | 0.11-0.33
Acepromazine | 1.1 | 0.5 | 30-60 | 1.1-2.2 | 0.11-0.22
Xylazine | 1.1 | 0.5 | 30-60 | 1.1-2.2 | 0.11-0.22
Oxymorphone | 1.1 | 0.5 | 30-60 | 1.1-2.2 | 0.11-0.22
Medetomidine | 1.1 | 0.5 | 30-60 | 1.1-2.2 | 0.11-0.22

Repeated maintenance doses of propofol do not result in increased recovery times, indicating that the anesthetic effects of propofol are not cumulative in dogs.

Maintenance Dosage Guidelines for Cats
Preanesthetic | Propofol Maintenance Dose |  | Propofol Rate of Administration
 | mg/kg | mg/lb | Seconds | mg/kg/min | mL/kg/min
None | 1.1-4.4 | 0.5-2.0 | 30-60 | 1.1-4.4 | 0.11-0.44
Acepromazine | 1.1-4.4 | 0.5-2.0 | 30-60 | 1.1-4.4 | 0.11-0.44
Butorphanol | 1.1-4.4 | 0.5-2.0 | 30-60 | 1.1-4.4 | 0.11-0.44
Oxymorphone | 1.1-4.4 | 0.5-2.0 | 30-60 | 1.1-4.4 | 0.11-0.44
Xylazine | 1.1-2.2 | 0.5-1.0 | 30-60 | 1.1-2.2 | 0.11-0.22
Acepromazine/Butorphanol | 1.1-3.3 | 0.5-1.5 | 30-60 | 1.1-3.3 | 0.11-0.33
Acepromazine/Oxymorphone | 1.1-3.3 | 0.5-1.5 | 30-60 | 1.1-3.3 | 0.11-0.33

Repeated maintenance doses of propofol may result in slightly increased recovery times, indicating that the anesthetic effects of propofol may be cumulative in cats.

B.Maintenance by Inhalant Anesthetics: Clinical trials using propofol have shown that it may be necessary to use a higher initial concentration of the inhalant anesthetic than is usually required following induction using barbiturate anesthetics, due to rapid recovery from Rapanofal® injection.

OVERDOSAGE

Rapid administration or accidental overdosage of Rapanofal® injection may cause neurologic and cardiopulmonary depression. Respiratory arrest (apnea) may be observed. In cases of respiratory depression, stop drug administration, establish a patent airway, and initiate assisted or controlled ventilation with oxygen. Cardiovascular depression should be treated with plasma expanders, pressor agents, antiarrhythmic agents or other techniques as appropriate for the observed abnormality.

In feline safety studies using healthy cats and elevated doses of propofol, unexplained decreases in albumin, globulin, and total protein values were noted. Increases in bile acids and triglycerides were also noted and were probably due to the lipid content of the drug formulation. These transient changes were not clinically significant in healthy cats.

CONTRAINDICATIONS

Rapanofal® injection is contraindicated in dogs and cats with a known hypersensitivity to propofol or its components, or when general anesthesia or sedation are contraindicated.

WARNINGS

Induction of anesthesia with Rapanofal® injection is frequently associated with apnea and respiratory depression. Hypotension and oxygen desaturation can occur also, especially following rapid bolus administration. Apnea is observed less frequently following maintenance doses of Rapanofal® injection when given as the sole maintenance agent, or when a maintenance dose is administered during inhalant anesthesia.

When using Rapanofal® injection, patients should be continuously monitored and facilities for the maintenance of a patent airway, artificial ventilation, and oxygen supplementation must be immediately available. The clinical use of propofol without available supplemental oxygen and artificial ventilation has not been adequately evaluated and is not recommended.

PRECAUTIONS

1.Rapanofal® injection contains no antimicrobial preservatives. Strict aseptic techniques must always be maintained during handling since the vehicle is capable of supporting rapid growth of microorganisms. Failure to follow aseptic handling procedures may result in microbial contamination causing fever, infection/sepsis, and/or other life-threatening illness. Do not use if contamination is suspected.

2.When using Rapanofal® injection, patients should be continuously monitored, and facilities for the maintenance of a patent airway, artificial ventilation, and oxygen supplementation must be immediately available. The clinical use of propofol without available supplemental oxygen and artificial ventilation has not been adequately evaluated and is not recommended.

3.Anesthesia effects: Careful monitoring of the patient is necessary when using Rapanofal® injection as a maintenance anesthetic due to the possibility of rapid arousal. Apnea may occur following maintenance doses of Rapanofal® injection.
Following induction, additional Rapanofal® injection at the lower maintenance dose may be needed to complete the transition to inhalant maintenance anesthesia due to rapid recovery from propofol. Doses administered during the transition to inhalant anesthesia or during inhalant maintenance anesthesia may result in apnea.

4.Physiological effects: During induction of anesthesia, mild hypotension and increased heart rate may occur when Rapanofal® injection is used alone.

5.Premedicants: Premedicants may increase the anesthetic or sedative effect of Rapanofal® injection and result in more pronounced changes in systolic, diastolic and mean arterial blood pressures. The use of ketamine (an approved compound for restraint in cats) is not recommended as a preanesthetic prior to propofol due to an increased number of patients experiencing apnea.

6.Breeding animals: Adequate data concerning the safe use of Rapanofal® injection in pregnant, lactating, and breeding dogs and cats have not been obtained. Propofol crosses the placenta, and as with other general anesthetic agents, the administration of propofol may be associated with neonatal depression.

7.Puppies and Kittens: The use of propofol has not been evaluated in puppies or kittens.

8.Compromised or debilitated dogs and cats: Doses may need adjustment for geriatric or debilitated patients. The administration of Rapanofal® injection to patients with renal failure and/or hepatic failure has not been evaluated. As with other anesthetic agents, caution should be exercised in dogs or cats with cardiac, respiratory, renal or hepatic impairment, or in hypovolemic or debilitated dogs and cats.

9.Sighthounds: Rapanofal® injection induction followed by inhalant anesthetic agents produced satisfactory anesthesia and recovery times in sighthounds. Propofol alone in 6 greyhounds and 7 non-greyhounds showed satisfactory, but longer recovery times in the greyhounds (averages of 47 and 18 minutes, respectively).^2 In a propofol pharmacokinetics study, greyhounds had higher propofol levels in plasma, a lower volume of distribution, slower total body clearance rates, and longer recovery times than did mixed-breed dogs. The elimination half-life was similar in both groups.^3

10.Arrhythmogenicity: In one study in dogs, propofol increased myocardial sensitivity to the development of epinephrine-induced ventricular arrhythmias in a manner similar to other anesthetics.^4

11.Consecutive day treatment: Heinz bodies increased dramatically in cats following repeat administration of propofol on consecutive days and were associated with decreases in RBC count and hematocrit. Large numbers of Heinz bodies can lead to hemolytic anemia.^5,6 In one study in cats, treatment with propofol once a day for 3 days led to a marked increase in Heinz bodies. Treatment for 5 or more consecutive days resulted in generalized malaise and/or facial edema; clinical signs of illness resolved within 24 to 48 hours after cessation of propofol.

12.Concurrent medication: No significant adverse interactions with commonly used drugs have been observed.

13.Perivascular administration: Perivascular administration does not produce local tissue reaction.

HUMAN USER SAFETY

Not for human use. Keep out of reach of children.

Rapanofal® injection should be managed to prevent the risk of diversion, through such measures as restriction of access and the use of drug accountability procedures appropriate to the clinical setting. Rare cases of self-administration of propofol have been reported, including dose-related fatalities.

Preventive care should be taken to avoid self-administration; for example, use of a guarded needle until the moment of injection is recommended. Symptoms of self-administration may include cardiovascular and/or respiratory depression. Anaphylaxis to propofol may occur during its first use, especially in patients with a history of drug allergy.^7 In the event of accidental self-administration, seek medical attention immediately.

Contact of this product with skin, eyes, and clothes should be avoided. If contact occurs, skin and eyes should be liberally flushed with water for 15 minutes. If irritation develops and continues, consult a physician.

Initial arousal following propofol anesthesia can be extremely rapid. Caution should be used at this time in manipulations involving the mouth, such as removing an endotracheal tube.

ADVERSE REACTIONS

The primary side effect of Rapanofal® injection is respiratory depression and apnea. Apnea was observed in 20% of the dog cases in the clinical trial. Apnea was observed in 1.4% of the cat cases in the clinical trial. All apnea cases responded satisfactorily to oxygen supplementation and/or controlled ventilation.

Apnea lasting less than 1 minute in healthy dogs or cats may cause no harm. Animals breathing atmospheric air that become apneic may show signs of cerebral damage after 2 minutes. Animals breathing 100% oxygen that become apneic may not show signs of cerebral damage for 5 to 8 minutes. Ventricular arrhythmias may occur secondary to hypoxia induced by apnea.

The primary side effect of Rapanofal® injection in cats is paddling during recovery. Paddling was observed in 11% of the cat cases in the clinical trial.

Other transient side effects in dogs or cats are observed infrequently or rarely:

•Respiratory: panting, reverse sneezing, cyanosis

•Musculoskeletal: paddling during recovery, tremors, tenseness, movements, fasciculations

•Cardiovascular: bradycardia, hypotension, cyanosis, tachycardia, premature ventricular contractions

•Central Nervous System: excitation, opisthotonus, seizure

•Injection Site: pain during injection

•Gastrointestinal: emesis/retching

•Other: rubbing at face or nose during recovery, vocalization during recovery, chewing or licking the injection site during recovery

CLINICAL PHARMACOLOGY

After a single dose, propofol blood level profiles are characterized by a rapid distribution phase and a rapid elimination phase. The liver is the main site of metabolism with the major portion of metabolites being excreted in urine. No change in pharmacokinetics occurs after multiple daily dosing in dogs. Concomitant medication may affect the pharmacokinetics of either propofol or other medications.

In dogs, Rapanofal® injection has been used in association with acepromazine, atropine, glycopyrrolate, halothane, isoflurane, medetomidine, oxymorphone, and xylazine. No pharmacological incompatibility has been encountered.

In cats, Rapanofal® injection has been used in association with acepromazine, atropine, glycopyrrolate, butorphanol, oxymorphone, xylazine, and halothane. No pharmacological incompatibility has been encountered.

To report suspected adverse drug events, call 1-888-621-0189. To obtain a copy of the Safety Data Sheet (SDS) or for technical assistance go to www.ivaoes.com.

For additional information about adverse drug experience reporting for animal drugs, Contact FDA at 1-888-FDA-VETS or www.fda.gov/reportanimalae.

STORAGE

Store between 4 – 25°C (40-77°F). Do not freeze.

Shake well before use. Discard opened vial with care. Within 6 hours after opening, any withdrawn unused product should be discarded safely.

HOW SUPPLIED

Rapanofal® injection is supplied in cartons of five-20 mL vials containing 10 mg propofol per mL.

REFERENCES

1.Thurman JC, Tranquilli WJ, Benson GJ, eds. Preanesthetics and anesthetic adjuncts. In: Lumb and Jones’ Veterinary Anesthesiology. 3rd ed; 1996: chap8.

2.Robertson SA, Johnson S, Beemsterboer J. Cardiopulmonary, anesthetic and postanesthetic effects of intravenous infusions of propofol in greyhounds and non-greyhounds. Am J Vet Res 53:1027-1032: 1992.

3.Zoran DL, Riedesel DH, Dyer DC. Pharmacokinetics of propofol in mixed-breed dogs and greyhounds. Am J Vet Res 54:755-760: 1993.

4.Kamibayashi T, Hayashi Y, Sumikawa K, Yamatodani A, Kawabata K, Yoshiya I. Enhancement by propofol of epinephrine-induced arrhythmias in dogs. Anesthesiology 75:1035-1040 1991.

5.Bush BM. Interpretation of laboratory results for small animal clinicians. Blackwell Science: 1996.

6.Andress JL, Day TK, Day DG. The effects of consecutive day propofol anesthesia on feline red blood cells. Veterinary Surgery 24:277-282:1995.

7.Laxenaire MC, Mata-Bermejo E, Moneret-Vautrin DA, Gueant JL. Life-threatening anaphylactoid reactions to propofol (DIPRIVAN®). Anesthesiology 77:275-280: 1992.

8.Plumb D. Veterinary Drug Handbook 2nd ed. pp. 455-458: 1995.

9.Branson, KR, Gross ME, Booth NH, Adams RH, ed. Veterinary Pharmacology and Therapeutics 7thed., pp. 299-300: 1995.

Net Contents: 20 mL

NDC 86064-001-20

Mfd. In Italy For:
Ivaoes Animal Health
Doral, FL 33126

Rev 10/25

PRINCIPAL LABEL DISPLAY PANEL

Carton Label

Front and Back Panel
NDC 86064-001-20
Net Contents: 5 x 20 mL
Rapanofal®(propofol injectable emulsion)
Anesthetic Injection
Each mL contains 10 mg propofol
CAUTION: Federal law restricts this drug to use
by or on the order of a licensed veterinarian
Approved by FDA under NADA # 141-070
FOR USE IN ANIMALS ONLY
IVAOES
ANIMAL HEALTH

Left Side Panel
Emulsion for intravenous use in dogs and cats.
Read package insert for complete product information.
Use strict aseptic technique. Contains no preservative.
Begin use promptly after removing entire vial contents.
Discard appropriately within 6 hours after opening.
Do not use if contamination is suspected.
Each mL contains propofol (10 mg), soybean oil (100 mg),
glycerol (22.5 mg), egg yolk phospholipid (12 mg) and sodium
metabisulfite (0.25 mg), with sodium hydroxide to adjust pH.
The propofol emulsion is isotonic and has a pH of 4.5-6.6.
Store between 4°C-25°C (40°-77°F). Do not freeze.
Shake well before use.
Made in Italy for Ivaoes Animal Health, Doral, FL 33126
Rev 10/25

Right Side Panel
For intravenous use in dogs and cats.
Uses: Rapanofal® (propofol injectable emulsion) is an injectable
anesthetic for use in dogs and cats as follows:
1. As a single injection to provide general anesthesia for
short procedures.
2. For induction and maintenance of general anesthesia
using incremental doses to effect.
3. For induction of general anesthesia where maintenance
is provided by inhalant anesthetics.
Read package insert for complete product information.
Contains no antimicrobial preservative.
Shake well before use. Remaining contents of a vial should be
discarded safely within 6 hours after opening.
Store between 4°C-25°C (40°-77°F). Do not freeze.

Vial label

NDC 86064-001-20

Rapanofal®
(propofol injectable emulsion)
Anesthetic Injection
Each mL contains 10 mg propofol.
CAUTION: Federal law restricts this drug to use by or on the order of a licensed veterinarian.
Net Contents: 20mL
Approved by FDA under NADA #141-070
Emulsion for intravenous use in dogs and cats.
Read package insert for complete product information.

Use strict aseptic technique.Contains no preservative.Begin use promptly
after removing emtire vial contents.Discard appropriately within 6 hours
after opening.Do not use use if contamination is suspected.
Each mL contains propofol (10 mg),soybean oil (100 mg), glycerol (22.5 mg), egg yolk phospholipid (12 mg) and sodium metabisulfite (0.25 mg), with sodium hydroxide to adjust pH. The propofol emulsion is isotonic and has a pH of 4.5-6.6.
Store between 4°C – 25°C (40-77°F). Do not freeze. Shake well before use.
Made in Italy for Ivaoes Animal Health, Doral, FL 33126 Rev 10/25

IVAOES ANIMAL HEALTH